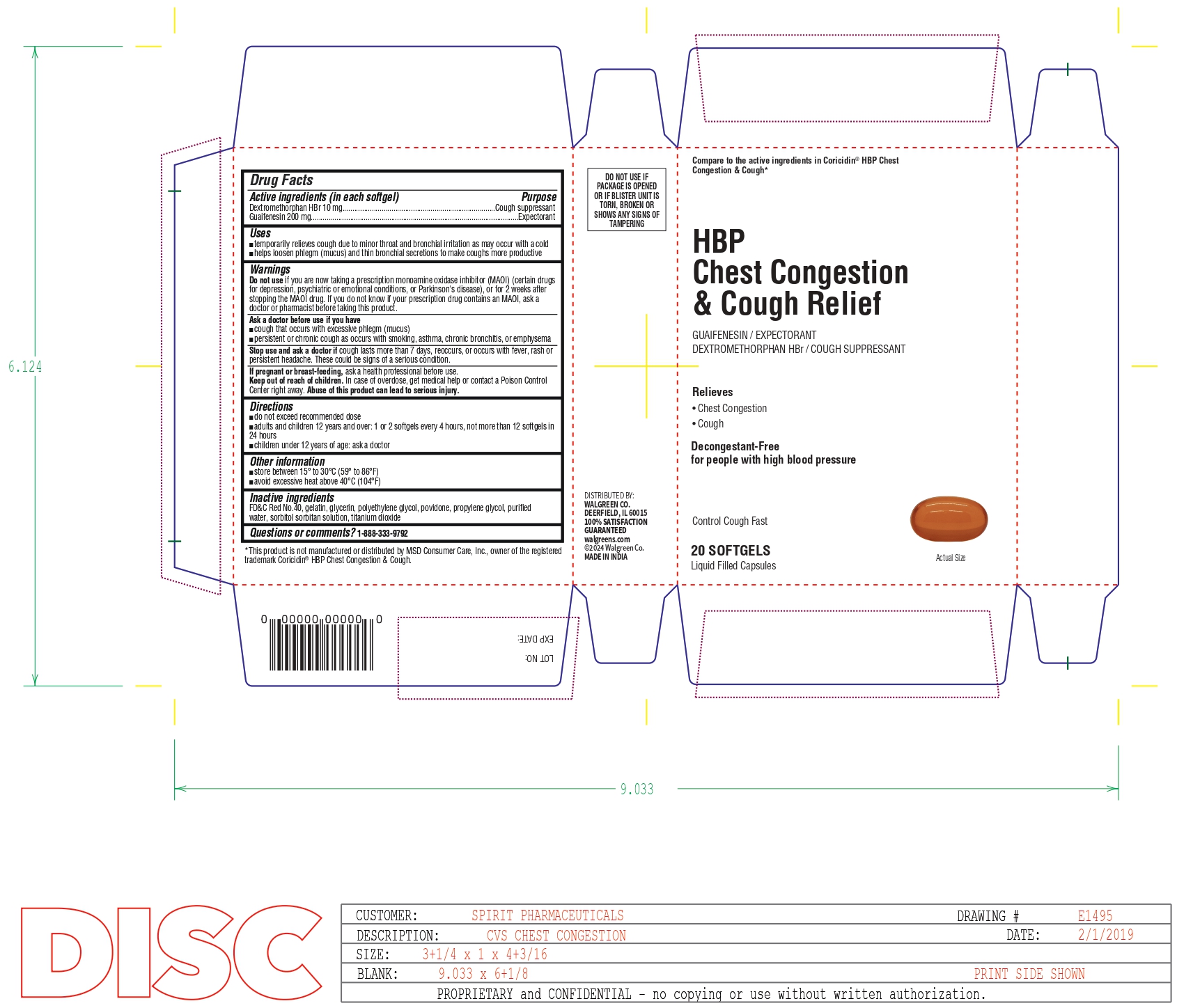 DRUG LABEL: HBP Chest Congestion and Cough Relief
NDC: 0363-6681 | Form: CAPSULE, LIQUID FILLED
Manufacturer: Walgreens
Category: otc | Type: HUMAN OTC DRUG LABEL
Date: 20260116

ACTIVE INGREDIENTS: DEXTROMETHORPHAN HYDROBROMIDE 10 mg/1 1; GUAIFENESIN 200 mg/1 1
INACTIVE INGREDIENTS: FD&C RED NO. 40; GELATIN; GLYCERIN; POLYETHYLENE GLYCOL, UNSPECIFIED; POVIDONE; PROPYLENE GLYCOL; WATER; SORBITOL SOLUTION; TITANIUM DIOXIDE

HBP Chest Congestion & Cough Relief